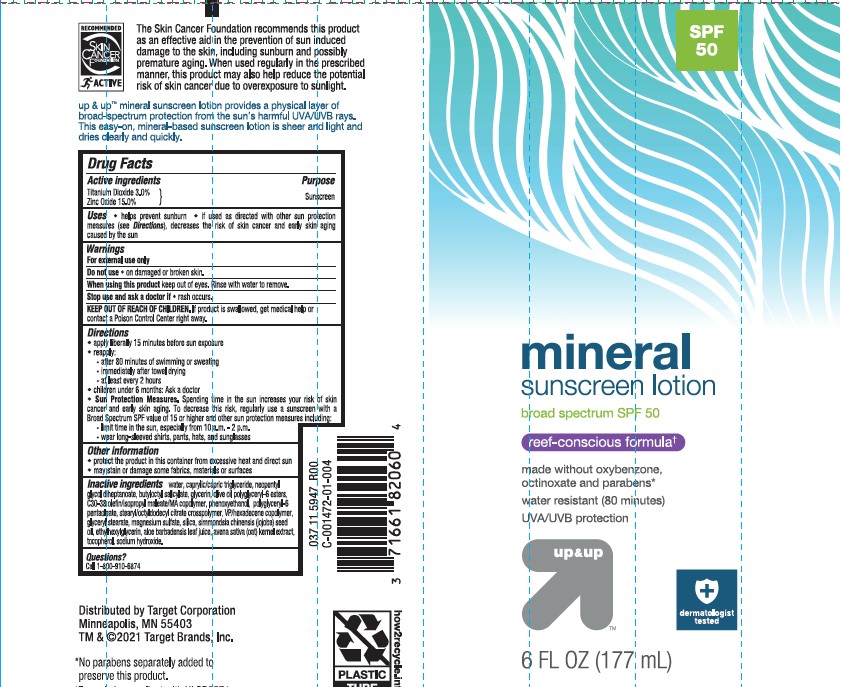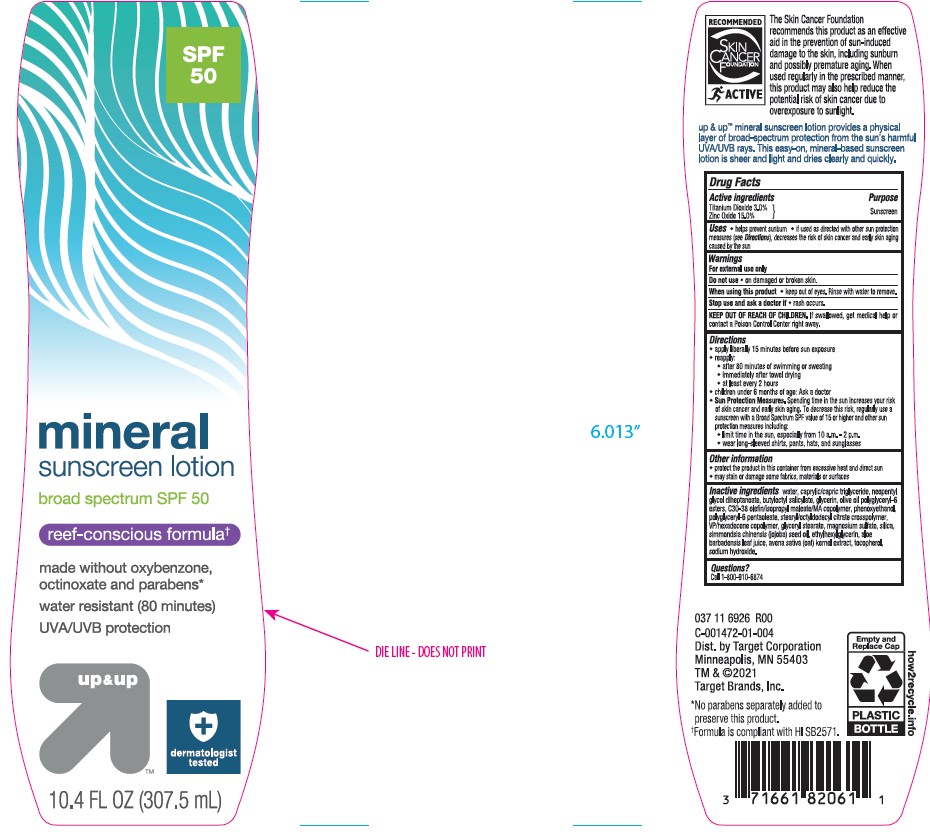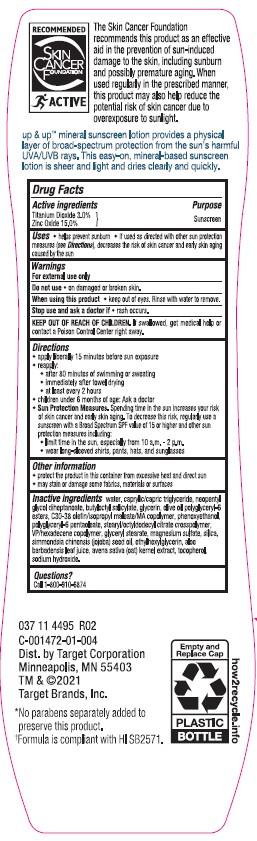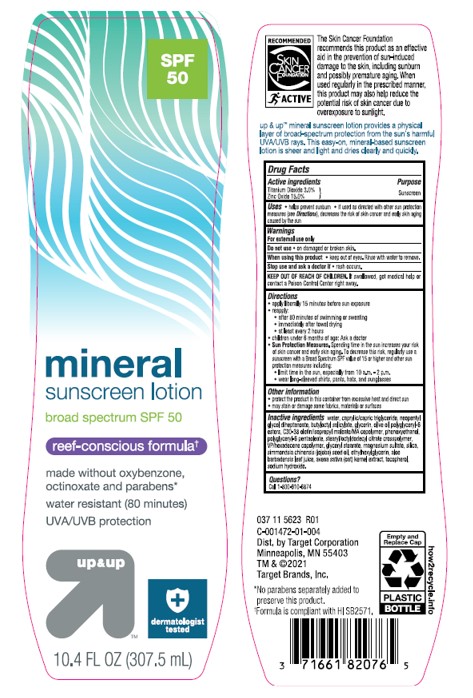 DRUG LABEL: Target Up and Up SPF 50 Mineral Sunscreen
NDC: 11673-233 | Form: LOTION
Manufacturer: TARGET CORPORATION
Category: otc | Type: HUMAN OTC DRUG LABEL
Date: 20241014

ACTIVE INGREDIENTS: ZINC OXIDE 150 mg/1 mL; TITANIUM DIOXIDE 30 mg/1 mL
INACTIVE INGREDIENTS: MAGNESIUM SULFATE HEPTAHYDRATE; NEOPENTYL GLYCOL DIHEPTANOATE; OLIVE OIL POLYGLYCERYL-6 ESTERS; ALOE VERA LEAF; GLYCERYL 1-STEARATE; OATMEAL; JOJOBA OIL; STEARYL/OCTYLDODECYL CITRATE CROSSPOLYMER; SODIUM HYDROXIDE; .ALPHA.-TOCOPHEROL, DL-; VINYLPYRROLIDONE/HEXADECENE COPOLYMER; WATER; MEDIUM-CHAIN TRIGLYCERIDES; GLYCERIN; SILICON DIOXIDE; PHENOXYETHANOL; BUTYLOCTYL SALICYLATE; ETHYLHEXYLGLYCERIN

Target Up & Up SPF 50 Mineral Sunscreen Lotion

Active ingredients

Titanium Dioxide 3.0%

Zinc Oxide 15.0%

Purpose

Sunscreen

Uses

• helps prevent sunburn • if used as directed with other sun protection measures (see Directions), decreases the risk of skin cancer and early skin aging caused by the sun

Warnings

For external use only

Do not use

• on damaged or broken skin

When using this product

• keep out of eyes. Rinse with water to remove.

Stop use and ask a doctor if

- rash occurs

Keep out of reach of children.

If swallowed, get medical help or contact a Poison Control Center right away.

Directions

• apply liberally 15 minutes before sun exposure

• reapply:

• after 80 minutes of swimming or sweating

• immediately after towel drying

• at least every 2 hours

• children under 6 months of age: Ask a doctor

- Sun Protection Measures. Spending time in the sun increases your risk of skin cancer and early skin aging. To decrease this risk, regularly use a sunscreen with a Broad Spectrum SPF value of 15 or higher and other sun protection measures including:

• limit time in the sun, especially from 10 a.m. - 2 p.m.

• wear long-sleeved shirts, pants, hats, and sunglasses

Other information

• protect the product in this container from excessive heat and direct sun

• may stain or damage some fabrics, materials or surfaces

Inactive ingredients

Water, Caprylic/Capric Triglyceride, Neopentyl Glycol Diheptanoate, Butyloctyl Salicylate, Glycerin, Olive Oil Polyglyceryl-6 Esters, C30-38 Olefin/Isopropyl Maleate/MA Copolymer, Phenoxyethanol, Polyglyceryl-6 Pentaoleate, Stearyl/Octyldodecyl Citrate Crosspolymer, VP/Hexadecene Copolymer, Glyceryl Stearate, Magnesium Sulfate, Silica, Simmondsia Chinensis (Jojoba) Seed Oil, Ethylhexylglycerin, Aloe Barbadensis Leaf Juice, Avena Sativa (Oat) Kernel Extract, Tocopherol, Sodium Hydroxide.